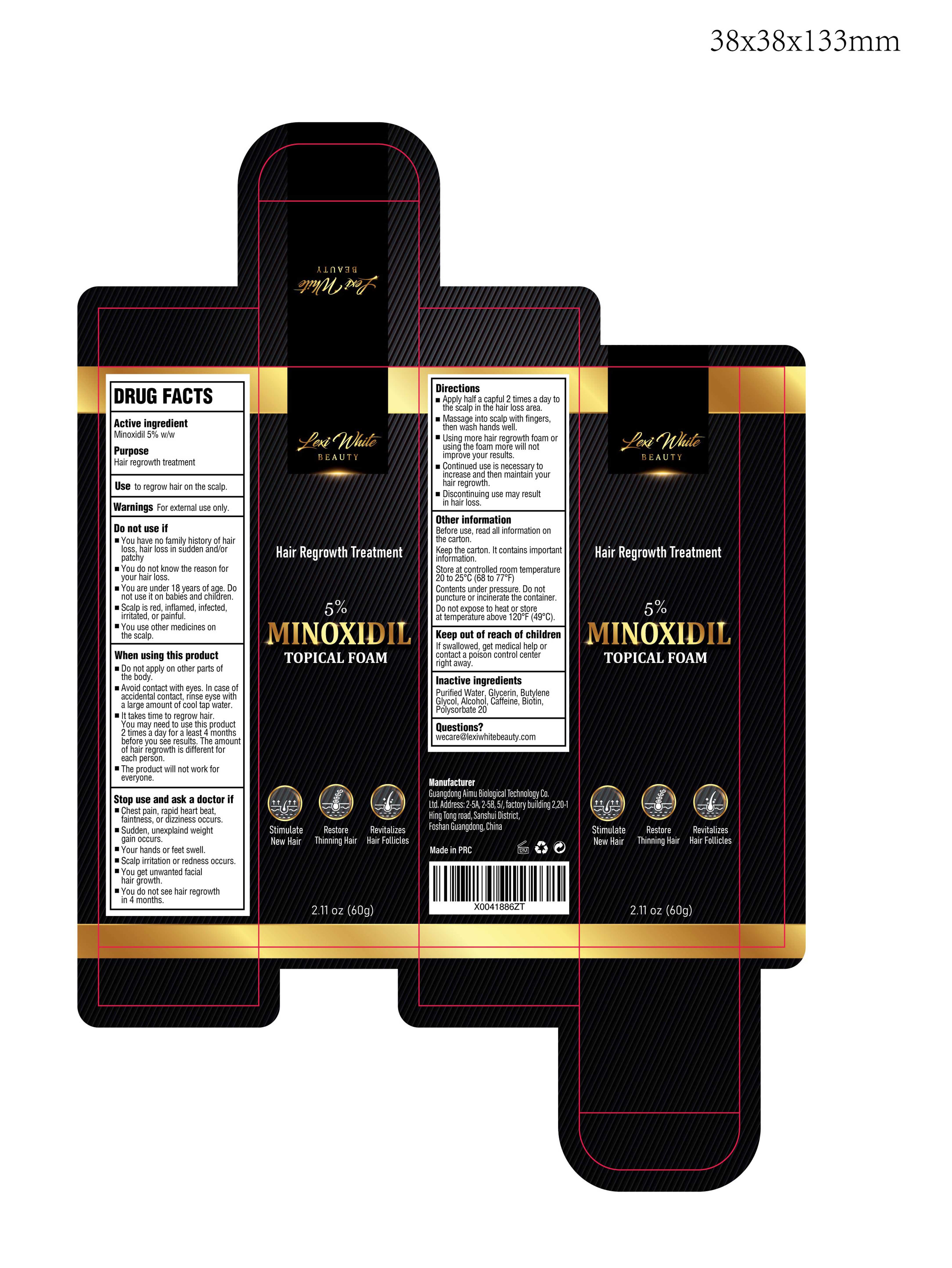 DRUG LABEL: Lexi White Beauty Hair Regrowth 5%  Minoxidil Foam
NDC: 83566-402 | Form: LIQUID
Manufacturer: Guangdong Aimu Biological Technology Co., Ltd
Category: otc | Type: HUMAN OTC DRUG LABEL
Date: 20240415

ACTIVE INGREDIENTS: MINOXIDIL 0.05 g/1 mL
INACTIVE INGREDIENTS: ALCOHOL; CAFFEINE; WATER; GLYCERIN; BUTYLENE GLYCOL; BIOTIN; POLYSORBATE 20

Lexi White Beauty Hair Regrowth 5% Minoxidil Foam

Lexi White Beauty Hair Regrowth 5% Minoxidil Foam

ACTIVE INGREDIENT

Minoxidil 5%

PURPOSE

Hair regrowth treatment

INDICATIONS AND USAGE

Use to regrow hair on the scalp.

WARNINGS

For external use only.

DO NOT USE

You have no family history of hair loss, hair loss in sudden and/or patchy.
You do not know the reason for your hair loss.
You are under 18 years of age. Do not use it on babies and children.
Scalp is red,inflamed, infected, irritated, or painful.
You use other medicines on the scalp.

WHEN USING

Do not apply on other parts of the body.

Avoid contact with eyes. In case of accidental contact,rinse evse with a large amount of cool tap water.

lt takes time to regrow hair. You may need to use this product 2 times a day for a least 4 months before you see results. The amount of hair regrowth is different for each person.

The product will not work for everyone.

STOP USE

Chest pain, rapid heart beat. faintness,or dizziness occurs.
Sudden, unexplaind weight gain occurs.
Your hands or feet swell.
Scalp irritation or redness occurs.
You get unwanted facial hair growth.
You do not see hair regrowth in 4 months.

KEEP OUT OF REACH OF CHILDREN

If swallowed, get medical help or contact a poison control center right away.

DOSAGE AND ADMINISTRATION

Apply half a capful 2 times a day to the scalp in the hair loss area.
Massage into scalp with fingers, then wash hands well.
Using more hair regrowth foam or using the foam more will not improve your results.
Continued use is necessary to increase and then maintain your hair regrowth.
Discontinuing use may result in hair loss.

STORAGE AND HANDLING

Before use, read all information onthe carton.
Keep the carton. lt contains importantinformation.
Store at controlled room temperature20 to 25°C (68 to 77°F).
Contents under pressure. Do notpuncture or incinerate the container.
Do not expose to heat or storeat temperature above 120°F (49°C).

INACTIVE INGREDIENT

WATER
Glycerin
Butylene Glycol
Alcohol
Caffeine
Biton
Polysorbate 20